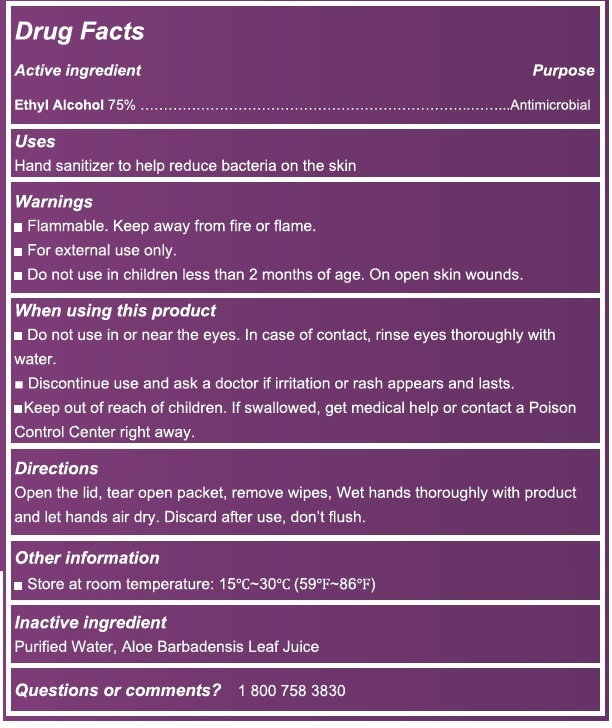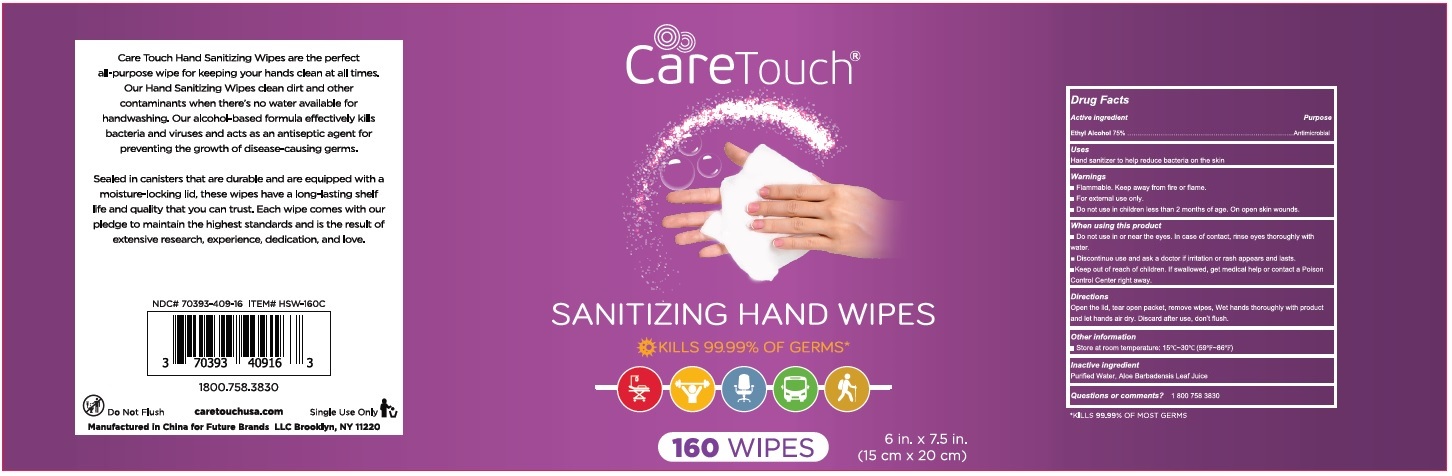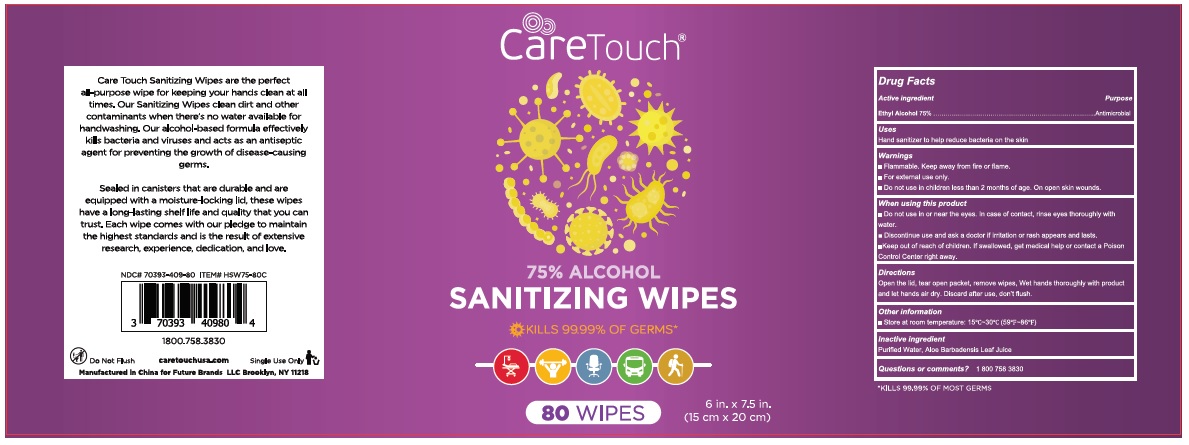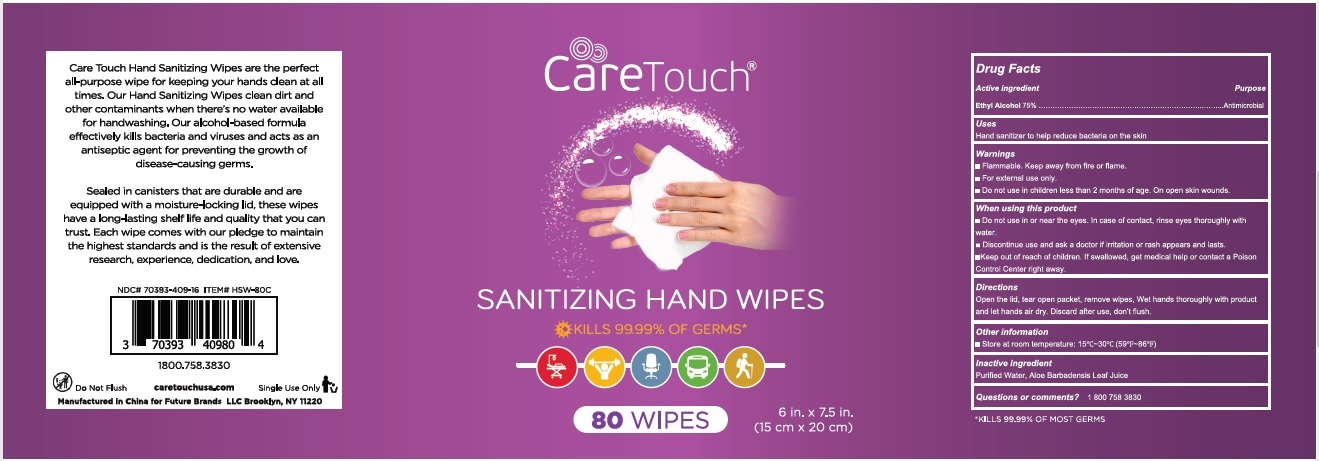 DRUG LABEL: Caretouch Sanitizing Hand Wipes
NDC: 70393-409 | Form: CLOTH
Manufacturer: Future Diagnostics Llc
Category: otc | Type: HUMAN OTC DRUG LABEL
Date: 20200925

ACTIVE INGREDIENTS: ALCOHOL 75 mL/100 mL
INACTIVE INGREDIENTS: WATER; ALOE VERA LEAF

CareTouch SANITIZING HAND WIPES

Active ingredient

Ethyl Alcohol 75%

Purpose

Antimicrobial

Uses

Hand Sanitizer to help reduce bacteria on the skin

Warnings

- Flammable. Keep away from fire or flame
- For external use only.
- Do not use in children less than 2 months of age. On open skin wounds.

When using this product

- Do not use in or near the eyes. In case of contact, rinse eyes thoroughly with water.
- Discontinue use and ask a doctor if irritation or rash appears and lasts.

Keep out of reach of children

If swallowed, get medical help or contact a Poison Control Center right away

Directions

Open the lid, tear open packet, remove wipes, Wet hands thoroughly with product and let hands air dry. Discard after use, don't flush.

Other information

- Store at room temperature: 15˚C~30˚C(59˚F~86˚F)

Inactive ingredient

Purified Water, Aloe Barbadensis Leaf Juice

Questions or comments?

1 800 758 3830

KILLS 99.99% OF GERMS*

Care Touch Hand Sanitizing Wipes are the perfect all-purpose wipe for keeping your hands clean at all times. Our Hand Sanitizing Wipes clean dirt and other contaminants when there's no water available for handwashing. Our alcohol-based formula effectively kills bacteria and viruses and acts as an antiseptic agent for preventing the growth of disease-causing germs.

Sealed in canisters that are durable and are equipped with a moisture-locking lid, these wipes have a long-lasting shelf life and quality that you can trust. Each wipe comes with our pledge to maintain the highest standards and is the result of extensive research, experience, dedication, and love.

Do Not Flush

caretouchusa.com

Single Use Only

Manufactures in China for Future Brands LLC Brooklyn, NY 11220

*KILLS 99.99% OF MOST GERMS